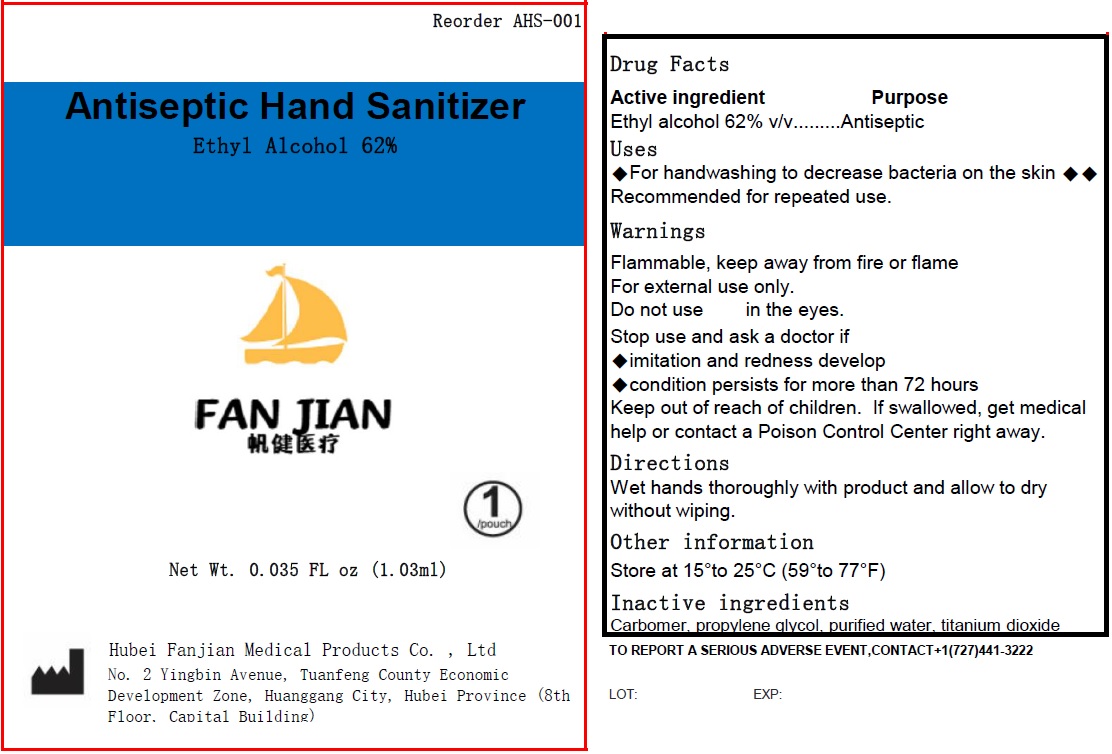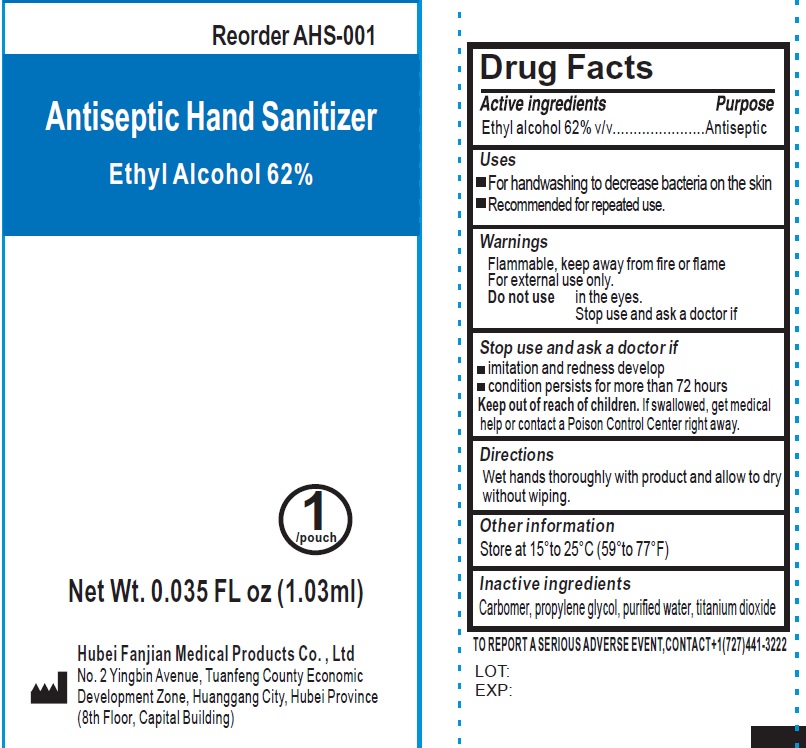 DRUG LABEL: Antiseptic Hand Sanitizer
NDC: 83165-000 | Form: LIQUID
Manufacturer: Hubei Fanjian Medical Product Co.,Ltd
Category: otc | Type: HUMAN OTC DRUG LABEL
Date: 20231110

ACTIVE INGREDIENTS: ALCOHOL 62 mL/100 mL
INACTIVE INGREDIENTS: CARBOMER HOMOPOLYMER, UNSPECIFIED TYPE; PROPYLENE GLYCOL; WATER; TITANIUM DIOXIDE

Antiseptic Hand Sanitizer

Active ingredients

Ethyl alcohol 62% v/v

Purpose

`Antiseptic

Uses

- For handwashing to decrease bacteria on the skin
- Recommended for repeated use.

Warnings

Flammable, keep away from fire or flame For external use only.

Do not use

in the eyes.

Stop use and ask a doctor if

- imitation and redness develop
- condition persists for more than 72 hours

Keep out of reach of children.

If swallowed, get medical help or contact a Poison Control Center right away.

Directions

Wet hands thoroughly with product and allow to dry without wiping.

Other information

Store at 15°to 25°C (59°to 77°F)

Inactive ingredients

Carbomer, propylene glycol, purified water, titanium dioxide